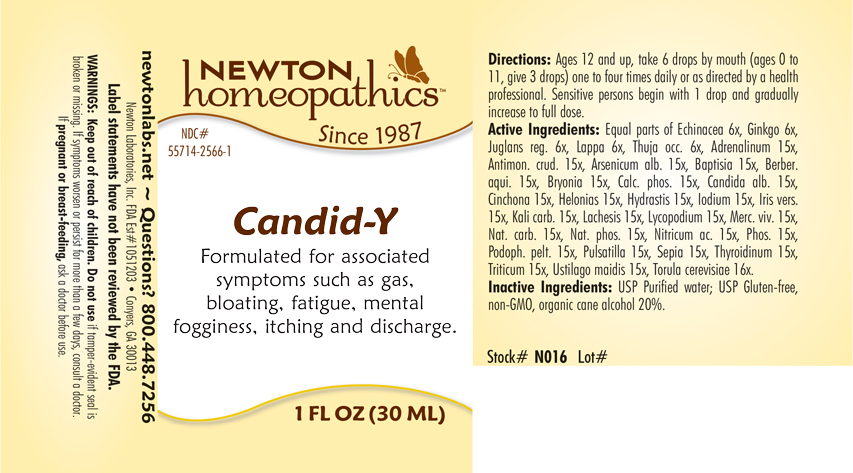 DRUG LABEL: Candid- Y
NDC: 55714-2566 | Form: LIQUID
Manufacturer: Newton Laboratories, Inc.
Category: homeopathic | Type: HUMAN OTC DRUG LABEL
Date: 20210201

ACTIVE INGREDIENTS: GINKGO 6 [hp_X]/1 mL; ENGLISH WALNUT 6 [hp_X]/1 mL; ARCTIUM LAPPA ROOT 6 [hp_X]/1 mL; THUJA OCCIDENTALIS LEAFY TWIG 6 [hp_X]/1 mL; EPINEPHRINE 15 [hp_X]/1 mL; CANDIDA ALBICANS 15 [hp_X]/1 mL; THYROID, UNSPECIFIED 15 [hp_X]/1 mL; SACCHAROMYCES CEREVISIAE 16 [hp_X]/1 mL; ELYMUS REPENS ROOT 15 [hp_X]/1 mL; USTILAGO MAYDIS 15 [hp_X]/1 mL; ANTIMONY TRISULFIDE 15 [hp_X]/1 mL; ARSENIC TRIOXIDE 15 [hp_X]/1 mL; BAPTISIA TINCTORIA 15 [hp_X]/1 mL; MAHONIA AQUIFOLIUM ROOT BARK 15 [hp_X]/1 mL; BRYONIA ALBA ROOT 15 [hp_X]/1 mL; TRIBASIC CALCIUM PHOSPHATE 15 [hp_X]/1 mL; CINCHONA OFFICINALIS BARK 15 [hp_X]/1 mL; CHAMAELIRIUM LUTEUM ROOT 15 [hp_X]/1 mL; GOLDENSEAL 15 [hp_X]/1 mL; IODINE 15 [hp_X]/1 mL; IRIS VERSICOLOR ROOT 15 [hp_X]/1 mL; POTASSIUM CARBONATE 15 [hp_X]/1 mL; LACHESIS MUTA VENOM 15 [hp_X]/1 mL; LYCOPODIUM CLAVATUM SPORE 15 [hp_X]/1 mL; MERCURY 15 [hp_X]/1 mL; SODIUM CARBONATE 15 [hp_X]/1 mL; SODIUM PHOSPHATE, DIBASIC, HEPTAHYDRATE 15 [hp_X]/1 mL; NITRIC ACID 15 [hp_X]/1 mL; SEPIA OFFICINALIS JUICE 15 [hp_X]/1 mL; PHOSPHORUS 15 [hp_X]/1 mL; PODOPHYLLUM 15 [hp_X]/1 mL; ANEMONE PULSATILLA 15 [hp_X]/1 mL; ECHINACEA, UNSPECIFIED 6 [hp_X]/1 mL
INACTIVE INGREDIENTS: WATER; ALCOHOL

Candid-Y 2566L

OTC - KEEP OUT OF REACH OF CHILDREN SECTION

Keep out of reach of children.

OTC - PREGNANCY OR BREAST FEEDING SECTION

If pregnant or breast-feeding, ask a doctor before use.

INACTIVE INGREDIENT SECTION

USP Purified water; USP Gluten-free, non-GMO, organic cane alcohol 20%

OTC - PURPOSE SECTION

Formulated for associated symptoms such as gas, bloating, fatigue, mental fogginess, itching, and discharge.

WARNINGS SECTION

WARNINGS: Keep out of reach of children. Do not use if tamper-evident seal is broken or missing. If symptoms worsen or persist for more than a few days, consult a doctor. If pregnant or breast-feeding, ask a doctor before use.

QUESTIONS SECTION

newtonlabs.net - Questions? 800 448-7256

Newton Laboratories, Inc. FDA Est # 1051203 - Conyers, GA 30013

OTC - ACTIVE INGREDIENT SECTION

Equal parts of Echinacea 6x, Ginkgo 6x, Juglans reg. 6x, Lappa 6x, Thuja occ. 6x, Antimon. crud. 15x, Baptisia 15x, Berber. aqui. 15x, Bryonia 15x, Calc. phos. 15x, Cinchona 15x, Helonias 15x, Hydrastis 15x, Iodium 15x, Iris vers. 15x, Kali carb. 15x, Lachesis 15x, Lycopodium 15x, Merc. viv. 15x, Nat.carb. 15x, Nat. phos. 15x, Nitricum ac. 15x, Phos. 15x, Podoph. pelt. 15x, Pulsatilla 15x, Sepia 15x, Adrenalinum 15x, Arsenium alb. 15x, Candida alb. 15x, Thyroidinum 15x, Triticum 15x, Ustilago maidis 15x, Torula cerevisiae 16x.

DOSAGE & ADMINISTRATION SECTION

Ages 12 and up, take 6 drops by mouth (ages 0 to 11, give 3 drops) one to four times daily or as directed by a health professional.

Sensitive persons begin with 1 drop and gradually increase to full dose.

INDICATIONS & USAGE SECTION

Formulated for associated symptoms such as gas, bloating, fatigue, mental fogginess, itching and discharge.